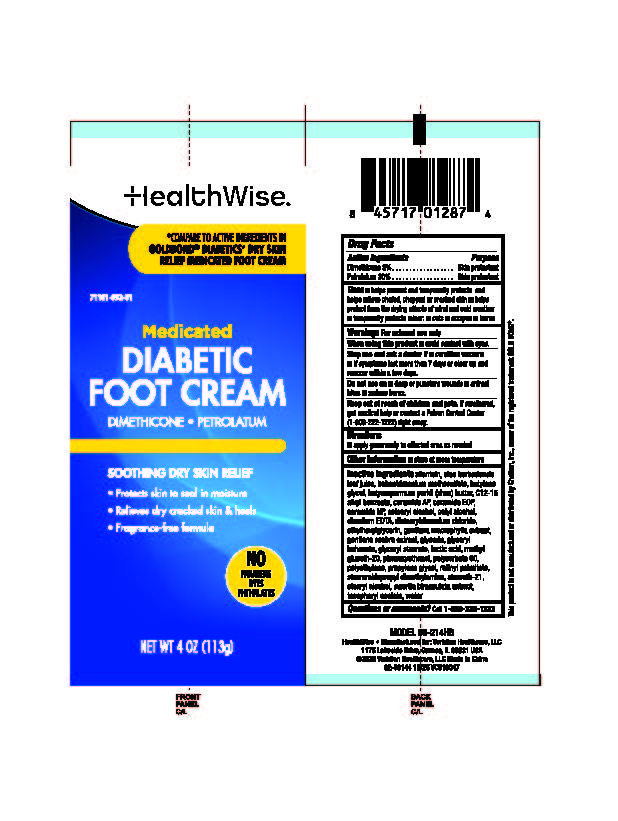 DRUG LABEL: HealthWise Diabetic Foot Cream
NDC: 71101-092 | Form: CREAM
Manufacturer: Veridian Healthcare
Category: otc | Type: HUMAN OTC DRUG LABEL
Date: 20251215

ACTIVE INGREDIENTS: PETROLATUM 30 g/100 g; DIMETHICONE 3 g/100 g
INACTIVE INGREDIENTS: GLYCERIN; CETOSTEARYL ALCOHOL; ALOE VERA LEAF; ALPHA-TOCOPHEROL ACETATE; WATER; BUTYLENE GLYCOL; PROPYLENE GLYCOL; GLYCERYL STEARATE; METHYL GLUCETH-20; POLYSORBATE 60; PHENOXYETHANOL; POLYETHYLENE; STEARYL ALCOHOL; STEARETH-21; CETYL ALCOHOL; STEARAMIDOPROPYL DIMETHYLAMINE; C12-15 ALKYL BENZOATE; DISTEARYLDIMONIUM CHLORIDE; BEHENTRIMONIUM METHOSULFATE; BUTYROSPERMUM PARKII (SHEA) BUTTER; EDETATE DISODIUM ANHYDROUS; ALLANTOIN; LACTIC ACID; GLYCERYL BEHENATE/EICOSADIOATE; ETHYLHEXYLGLYCERIN; RETINYL PALMITATE; SWERTIA BIMACULATA WHOLE; GENTIANA MACROPHYLLA ROOT; GENTIANA SCABRA WHOLE; CERAMIDE NP; CERAMIDE AP; CERAMIDE EOS

HealthWise Diabetic Foot Cream

Active Ingredient

Dimethicone 3%..............................Skin Protectant

Petrolatum 30%..............................Skin Protectant

Purpose

Skin Protectant

Uses

■helps prevent and temporarily protects and helps relieve chafed, chapped or cracked skin

■helps protect from the drying effects of wind and cold weather

■ temporarily protects minor: cuts, scrapes and burns

Warnings

For external use only.

When using this product

avoid contact with eyes.

Stop use and ask physician if

- condition worsens
- if symptoms last more than 7 days or clear up and occur again within a few days

Do not use on

- deep or puncture wounds
- animal bites
- serious burns

Keep out of reach of children and pets

If swallowed, get medical help or contact a Poison Control Center (1-800-222-1222) right away.

Directions

Apply generously to affected area as needed.

Other information

Store at room temperature

Inactive Ingredients

allantoin,aloe barbadensis leaf juice, behentrimonium methosulfate, butylene glycol, butyrospermum parkii (shea) butter, C12-15 alkyl benzoate, ceramide AP,ceramide EOP, ceramide NP,cetearyl alcohol,cetyl alcohol, disodium EOTA, distearyldimonium chloride, ethylhexylglycerin,gentiana macrophylla extract, gentiana scabra extract,glycerin, glyceryl behenate,glyceryl stearate, lactic acid, methyl gluceth-20, phenoxyethanol, polysorbate 60, polyethylene, propylene glycol, retinyl palmitate, stearamidopropyl dimethylamine,steareth-21, stearyl alcohol, swertia bimaculata extract, tocopheryl acetate, water

Questions?

Call 1-866-326-1313